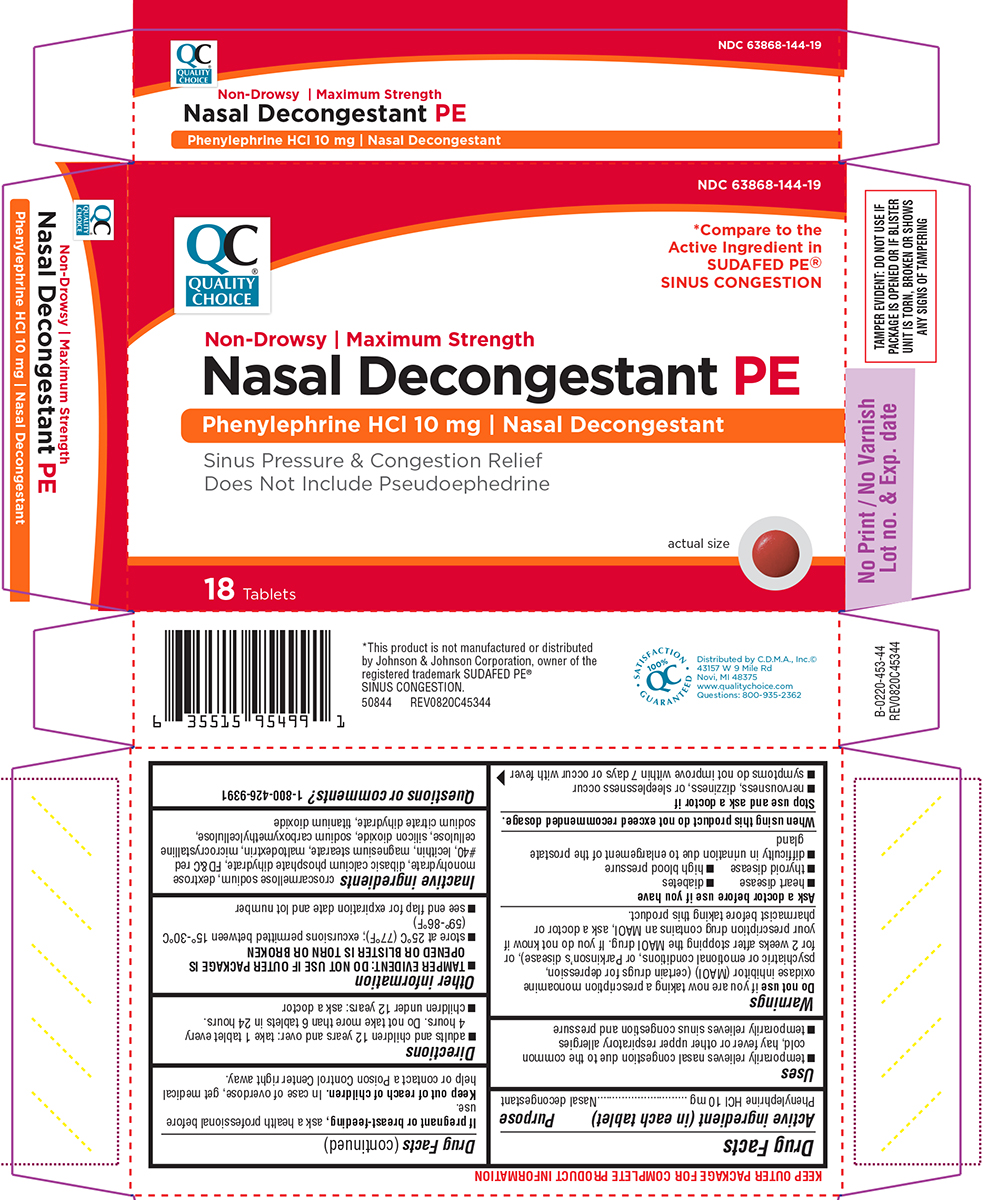 DRUG LABEL: Nasal Decongestant PE
NDC: 63868-144 | Form: TABLET, FILM COATED
Manufacturer: CHAIN DRUG MARKETING ASSOCIATION INC
Category: otc | Type: HUMAN OTC DRUG LABEL
Date: 20260112

ACTIVE INGREDIENTS: PHENYLEPHRINE HYDROCHLORIDE 10 mg/1 1
INACTIVE INGREDIENTS: CROSCARMELLOSE SODIUM; DEXTROSE MONOHYDRATE; DIBASIC CALCIUM PHOSPHATE DIHYDRATE; FD&C RED NO. 40; LECITHIN, SOYBEAN; MAGNESIUM STEARATE; MALTODEXTRIN; MICROCRYSTALLINE CELLULOSE; SILICON DIOXIDE; CARBOXYMETHYLCELLULOSE SODIUM, UNSPECIFIED; TRISODIUM CITRATE DIHYDRATE; TITANIUM DIOXIDE

Quality Choice 44-453-Delisted

Active ingredient (in each tablet)

Phenylephrine HCl 10 mg

Purpose

Nasal decongestant

Uses

- temporarily relieves nasal congestion due to the common cold, hay fever or other upper respiratory allergies
- temporarily relieves sinus congestion and pressure

Warnings

Do not use

if you are now taking a prescription monoamine oxidase inhibitor (MAOI) (certain drugs for depression, psychiatric or emotional conditions, or Parkinson's disease), or for 2 weeks after stopping the MAOI drug. If you do not know if your prescription drug contains an MAOI, ask a doctor or pharmacist before taking this product.

Ask a doctor before use if you have

- heart disease
- diabetes
- thyroid disease
- high blood pressure
- difficulty in urination due to enlargement of the prostate gland

When using this product

do not exceed recommended dosage.

Stop use and ask a doctor if

- nervousness, dizziness, or sleeplessness occur
- symptoms do not improve within 7 days or occur with fever

If pregnant or breast-feeding,

ask a health professional before use.

Keep out of reach of children.

In case of overdose, get medical help or contact a Poison Control Center right away.

Directions

- adults and children 12 years and over: take 1 tablet every 4 hours. Do not take more than 6 tablets in 24 hours.
- children under 12 years: ask a doctor

Other information

- TAMPER EVIDENT: DO NOT USE IF OUTER PACKAGE IS OPENED OR BLISTER IS TORN OR BROKEN
- store at 25ºC (77ºF); excursions permitted between 15º-30ºC (59º-86ºF)
- see end flap for expiration date and lot number

Inactive ingredients

croscarmellose sodium, dextrose monohydrate, dibasic calcium phosphate dihydrate, FD&C red #40, lecithin, magnesium stearate, maltodextrin, microcrystalline cellulose, silicon dioxide, sodium carboxymethylcellulose, sodium citrate dihydrate, titanium dioxide

Questions or comments?

1-800-426-9391

Principal Display Panel

QC®
QUALITY
CHOICE

NDC 63868-144-19

*Compare to the
Active Ingredient in
SUDAFED PE®
SINUS CONGESTION

Non-Drowsy | Maximum Strength
Nasal Decongestant PE
Phenylephrine HCl 10 mg | Nasal Decongestant

Sinus Pressure & Congestion Relief
Does Not Include Pseudoephedrine

18 Tablets

actual size

TAMPER EVIDENT: DO NOT USE IF
PACKAGE IS OPENED OR IF BLISTER
UNIT IS TORN, BROKEN OR SHOWS
ANY SIGNS OF TAMPERING

*This product is not manufactured or distributed
by Johnson & Johnson Corporation, owner of the
registered trademark SUDAFED PE®
SINUS CONGESTION.
50844 REV0820C45344

Distributed by C.D.M.A., Inc.©
43157 W 9 Mile Rd
Novi, MI 48375
www.qualitychoice.com
Questions: 800-935-2362

Quality Choice 44-453